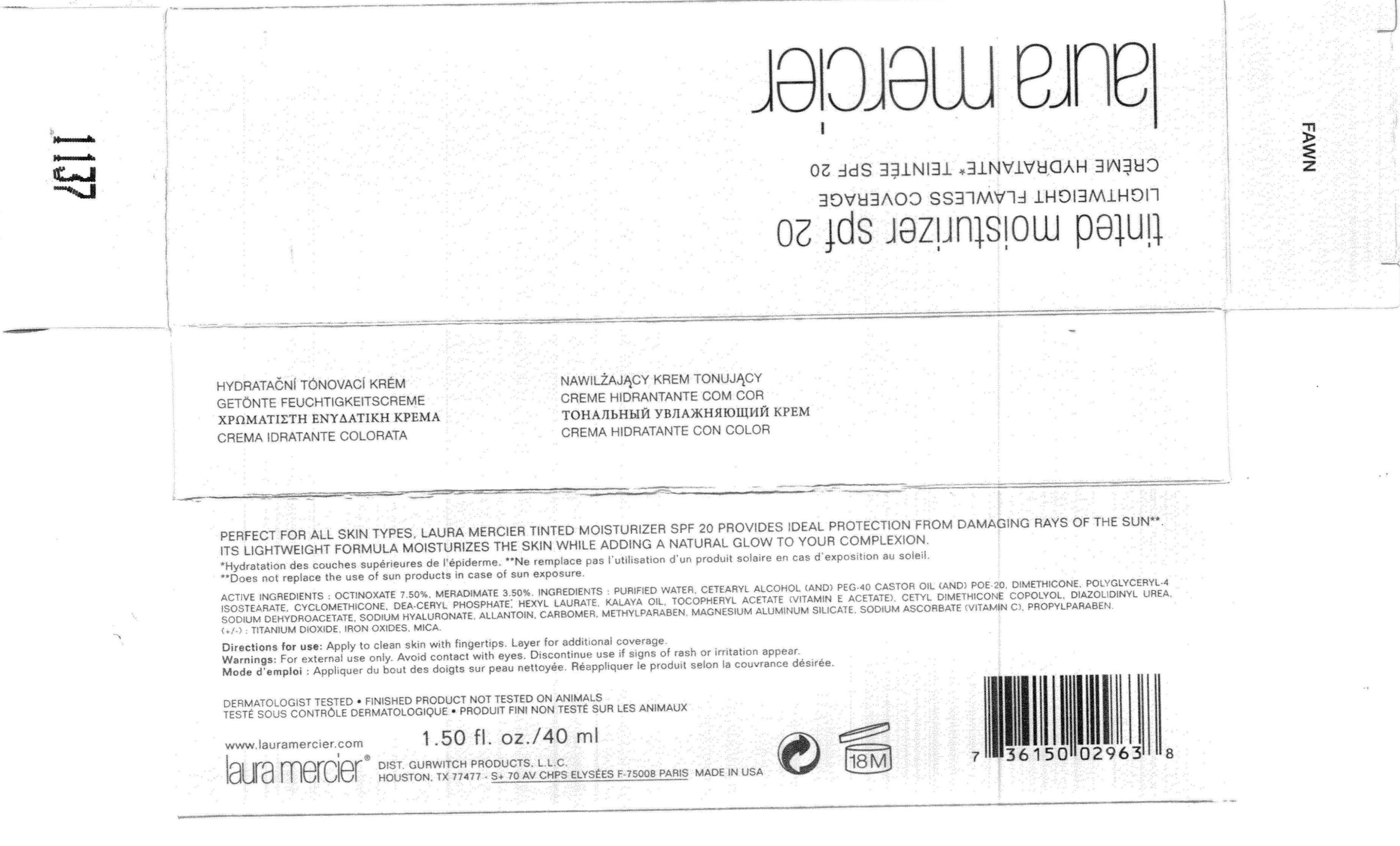 DRUG LABEL: Laura mercier Tinted Moisturizer SPF-20 Fawn
NDC: 65342-2963 | Form: CREAM
Manufacturer: Gurwitch Products, L.L.C.
Category: otc | Type: HUMAN OTC DRUG LABEL
Date: 20110502

ACTIVE INGREDIENTS: Octinoxate 3 mg/40 mg; MERADIMATE 1.4 mg/40 mg
INACTIVE INGREDIENTS: Water; Dimethicone; POLYGLYCERYL-4 ISOSTEARATE; CETOSTEARYL ALCOHOL; POLYOXYL 40 CASTOR OIL; HEXYL LAURATE; .ALPHA.-TOCOPHEROL ACETATE, D-; SODIUM DEHYDROACETATE; HYALURONATE SODIUM; ALLANTOIN; METHYLPARABEN; MAGNESIUM ALUMINUM SILICATE; SODIUM ASCORBATE; PROPYLPARABEN; TITANIUM DIOXIDE; DIAZOLIDINYL UREA; FERRIC OXIDE RED; MICA

ACTIVE INGREDIENT

Octinoxate (7.5%) , Meradimate (3.5%)

WARNINGS

WARNINGS : AFOR EXTERNAL USE ONLY. AVOID CONTACT WITH EYES. DISCONTINUE USE IF SIGNS OF RASH OR IRRITATION APPEAR.

Keep out of reach of children.

INDICATIONS AND USAGE

Direction for use : Apply to cleansed skin with fingertips. Layer fro additional coverage.

INACTIVE INGREDIENT

Ingredients : Purified Water , Cetearyl Alcohol (And) PEG-40 Castor Oil (And) POE-20 , Dimethicone ,Polyglyceryl-4 Isostearate ,Cyclomethicone , DEA-Ceryl Phospate, Hexyl Laurate ,Kalaya Oil , Tocopheryl Acetate ,Cetyl Dimethicone Copolyol , Diazolidinyl Urea, Sodium Dehydroacetate ,Sodium Hyaluronate , Allantoin ,Carbomer Methylparaben, Magensium Aluminum Silicate , Sodium Ascorbate, Propylparaben, (+/-) Titanium Dioxide , Iron Oixde , Mica